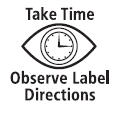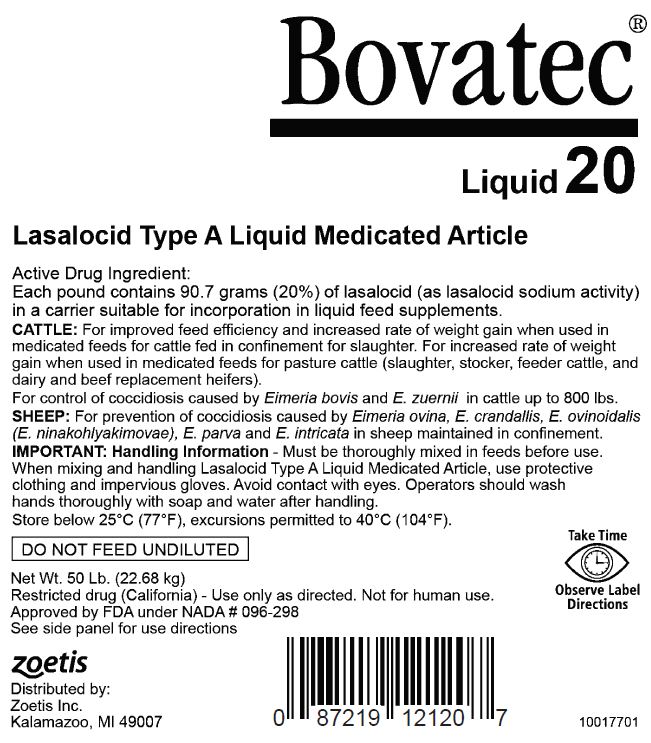 DRUG LABEL: Bovatec 20
NDC: 54771-1459 | Form: LIQUID
Manufacturer: Zoetis Inc.
Category: animal | Type: OTC TYPE A MEDICATED ARTICLE ANIMAL DRUG LABEL
Date: 20210104

ACTIVE INGREDIENTS: LASALOCID SODIUM 90.7 g/0.45 kg

Bovatec® Liquid 20

Bovatec Liquid 20

Lasalocid Type A Liquid Medicated Article

Active Drug Ingredient

Each pound contains 90.7 grams (20%) of lasalocid (as lasalocid sodium activity) in a carrier suitable for incorporation in liquid feed supplements.

VETERINARY INDICATIONS

CATTLE: For improved feed efficiency and increased rate of weight gain when used in medicated feeds for cattle fed in confinement for slaughter. For increased rate of weight gain when used in medicated feeds for pasture cattle (slaughter, stocker, feeder cattle, and dairy and beef replacement heifers).

For control of coccidiosis caused by Eimeria bovis and E. zuernii in cattle up to 800 lbs.

SHEEP: For prevention of coccidiosis caused by Eimeria ovina, E. crandallis, E. ovinoidalis (E. ninakohlyakimovae), E. parva and E. intricata in sheep maintained in confinement.

SAFE HANDLING WARNING

IMPORTANT: Handling Information - Must be thoroughly mixed in feeds before use. When mixing and handling Lasalocid Type A Liquid Medicated Article use protective clothing and impervious gloves. Avoid contact with eyes. Operators should wash hands thoroughly with soap and water after handling.

MIXING DIRECTIONS

This product should be incorporated into liquid feed supplements:

(1) Agitate Bovatec Liquid 20 before use.

(2) Supplements with suspending agent(s) should be in a pH range of 4 - 8 and maintain physical stability for up to three months with a viscosity not less than 300 cps.

(3) Conventional liquid supplements should be in a pH range of 4 - 8.

For liquid feeds stored in recirculating tank systems: Recirculate immediately prior to use for no less than 10 minutes, moving not less than 1 percent of the tank contents per minute from the bottom of the tank to the top. Recirculate daily as described even when not used.

For liquid feeds stored in mechanical, air, or other agitation-type tank systems: Agitate immediately prior to use for not less than 10 minutes, creating a turbulence at the bottom of the tank that is visible at the top. Agitate daily as described even when not used.

(4) The following is provided as a guide in determining the quantity of Bovatec Liquid 20 (Type A Medicated Article) to be added in preparing liquid feed supplements (LFS). Preparation of intermediate liquid preblend is not recommended.

LFS TO BE FED UNDILUTED
As a Type C Medicated Feed - Hand-Fed or Top Dressed
Amount of LFS to be fed (lbs/head/day) | To achieve a lasalocid intake of (mg/head/day) | Bovatec Liquid 20 per ton LFS
Amount of LFS to be fed (lbs/head/day) | To achieve a lasalocid intake of (mg/head/day) | pounds | fluid ounces [6.13 gm lasalocid per fluid ounce (Bovatec Liquid 20 specific gravity is 1.035)]
0.5 | 15 | 0.66 | 9.8
0.5 | 60 | 2.65 | 39.2
0.5 | 70 | 3.09 | 45.7
0.5 | 200 | 8.82 | 130.5
0.5 | 300 | 13.23 | 195.8
0.5 | 360 | 15.88 | 234.9
1.0 | 15 | 0.33 | 4.9
1.0 | 60 | 1.32 | 19.6
1.0 | 70 | 1.54 | 22.8
1.0 | 200 | 4.41 | 65.3
1.0 | 300 | 6.62 | 97.9
1.0 | 360 | 7.94 | 117.5
LFS TO BE DILUTED
As a Type B Medicated Feed - Mixed into a Feed
Amount of LFS to be added to final feed (lbs/ton) | Lasalocid in final feed (grams/ton) | Bovatec Liquid 20 per Ton LFS
Amount of LFS to be added to final feed (lbs/ton) | Lasalocid in final feed (grams/ton) | pounds | fluid ounces
100 | 10 | 2.21 | 32.6
100 | 25 | 5.51 | 81.6
100 | 30 | 6.62 | 97.9
150 | 10 | 1.47 | 21.8
150 | 25 | 3.68 | 54.4
150 | 30 | 4.41 | 65.3
200 | 10 | 1.10 | 16.3
200 | 25 | 2.76 | 40.8
200 | 30 | 3.31 | 48.9

DO NOT FEED UNDILUTED

USE DIRECTIONS

Species | Dose | Indications for use
Cattle Fed in Confinement for Slaughter | 10-30 grams lasalocid per ton of total ration (90% dry matter) | For improved feed efficiency in cattle being fed in confinement for slaughter, feed continuously to provide not less than 100 mg nor more than 360 mg per head per day.
 | 25-30 grams lasalocid per ton of total ration (90% dry matter) | For improved feed efficiency and increased rate of weight gain in cattle being fed in confinement for slaughter, feed continuously to provide not less than 250 mg nor more than 360 mg per head per day.
Pasture Cattle – slaughter, stocker, feeder cattle, and dairy and beef replacement heifers | 60-300 mg lasalocid per head/day | For increased rate of weight gain. The drug must be contained in at least 1 pound of feed and fed continuously on a daily basis.
Pasture Cattle – slaughter, stocker, feeder cattle, and dairy and beef replacement heifers | 60-300 mg lasalocid per head/day | For increased rate of weight gain, feed continuously on a free-choice basis. A feed mill license is required when the free-choice feed is manufactured using a proprietary formula and/or specifications. Free-choice feed formulations must be FDA-approved.
Pasture Cattle – slaughter, stocker, feeder cattle, and dairy and beef replacement heifers |  | Daily lasalocid intakes in excess of 200 mg per head per day have not been shown to be more effective than 200 mg lasalocid per head per day.
Pasture Cattle – slaughter, stocker, feeder cattle, and dairy and beef replacement heifers |  | NOTE: Coccidiosis may occur when young pasture cattle are co-mingled with adult cattle passing coccidial oocysts.
Cattle | 1 mg lasalocid per 2.2 lbs body weight/day | For control of coccidiosis caused by Eimeria bovis and E. zuernii in cattle up to 800 lbs. Hand feed continuously to provide not more than 360 mg per day.
Sheep | 20-30 grams lasalocid per ton of total ration (90% dry matter) | For prevention of coccidiosis caused by Eimeria ovina, E. crandallis, E. ovinoidalis (E. ninakohlyakimovae), E. parva, and E. intricata in sheep maintained in confinement. Feed continuously to provide not less than 15 mg nor more than 70 mg per head per day depending on body weight.

CAUTION

Animal Safety - Feeding undiluted or mixing errors resulting in excessive concentrations of lasalocid could be fatal to cattle and sheep.Do not allow horses or other equines access to Type A articles or Type B feeds containing lasalocid, as ingestion may be fatal. Safety of lasalocid for use in unapproved species has not been established.

Withdrawal Periods and Residue Warnings

No withdrawal period is required when used according to labeling.
A withdrawal period has not been established for this product in pre-ruminating calves.
Do not use in calves to be processed for veal.

Store below 25ºC (77ºF), excursions permitted to 40ºC (104ºF).

DO NOT FEED UNDILUTED

Net Wt. 50 Lb. (22.68 kg)

Restricted drug (California) - Use only as directed. Not for human use.
Approved by FDA under NADA # 096-298
See side panel for use directions

zoetis
Distributed by:
Zoetis Inc
Kalamazoo, MI 49007
10017701